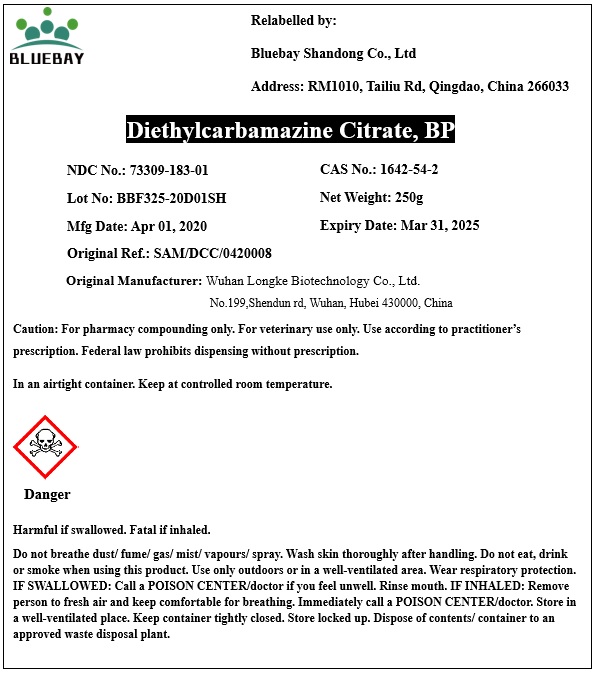 DRUG LABEL: Diethylcarbamazine Citrate
NDC: 73309-183 | Form: POWDER
Manufacturer: BLUEBAY SHANDONG CO.,LTD
Category: other | Type: BULK INGREDIENT
Date: 20200902

ACTIVE INGREDIENTS: DIETHYLCARBAMAZINE CITRATE 1 g/1 g

Diethylcarbamazine Citrate